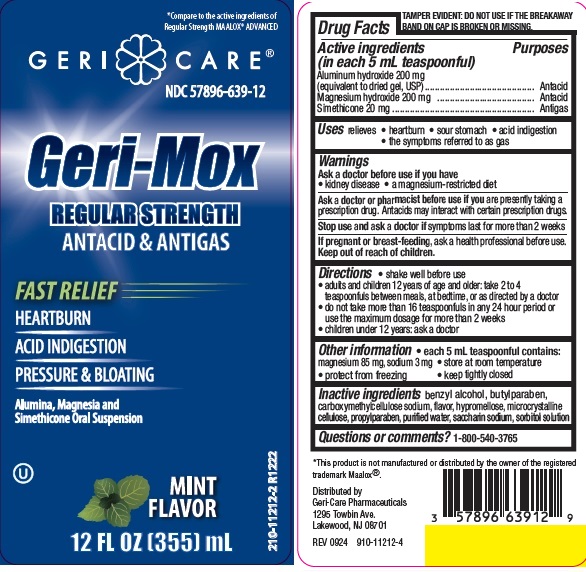 DRUG LABEL: GERI-MOX ANTACID ANTIGAS
NDC: 57896-639 | Form: SUSPENSION
Manufacturer: Geri-Care Pharmaceuticals, Corp
Category: otc | Type: HUMAN OTC DRUG LABEL
Date: 20251120

ACTIVE INGREDIENTS: ALUMINUM HYDROXIDE 200 mg/5 mL; MAGNESIUM HYDROXIDE 200 mg/5 mL; DIMETHICONE 20 mg/5 mL
INACTIVE INGREDIENTS: BENZYL ALCOHOL; BUTYLPARABEN; CARBOXYMETHYLCELLULOSE SODIUM; HYPROMELLOSES; CELLULOSE, MICROCRYSTALLINE; PROPYLPARABEN; WATER; SACCHARIN SODIUM; SORBITOL SOLUTION

geri-mox

Active ingredients (in each 5 mL teaspoonful)

Aluminum hydroxide 200 mg (equivalent to dried gel, USP)
Magnesium hydroxide 200 mg
Simethicone 20mg

Purposes

Antacid
Antigas

Uses

relieves

- heartburn
- sour stomach
- acid indigestion
- the symptoms referred to as gas

Warnings

Ask a doctor before use if you have

- kidney disease
- a magnesium-restricted diet

Ask a doctor or pharmacist before use if you are presently taking a prescription drug.
Antacids may interact with certain prescription drugs.
Stop use and ask a doctor if symptoms last more than 2 weeks
If pregnant or breast-feeding, ask a health professional before use.

Keep out of reach of children.

Directions

- shake well before use
- adults and children 12 years of age and older: take 2 to 4 teaspoonfuls between meals, at bedtime, or as directed by a doctor
- do not take more than 16 teaspoonfuls in any 24 hour period or use the maximum dosage for more than 2 weeks
- children under 12 years: ask a doctor

Other information

- each 5 mL teaspoonful contains: magnesium 85 mg, sodium 3 mg
- store at room temperature
- protect from freezing
- keep tightly closed

Inactive ingredients

benzyl alcohol, butylparaben, carboxymethylcellulose sodium, flavor, hypromellose, microcrystalline cellulose, propylparaben, purified water, saccharin sodium, sorbitol solution

Questions or comments?

1-800-540-3765